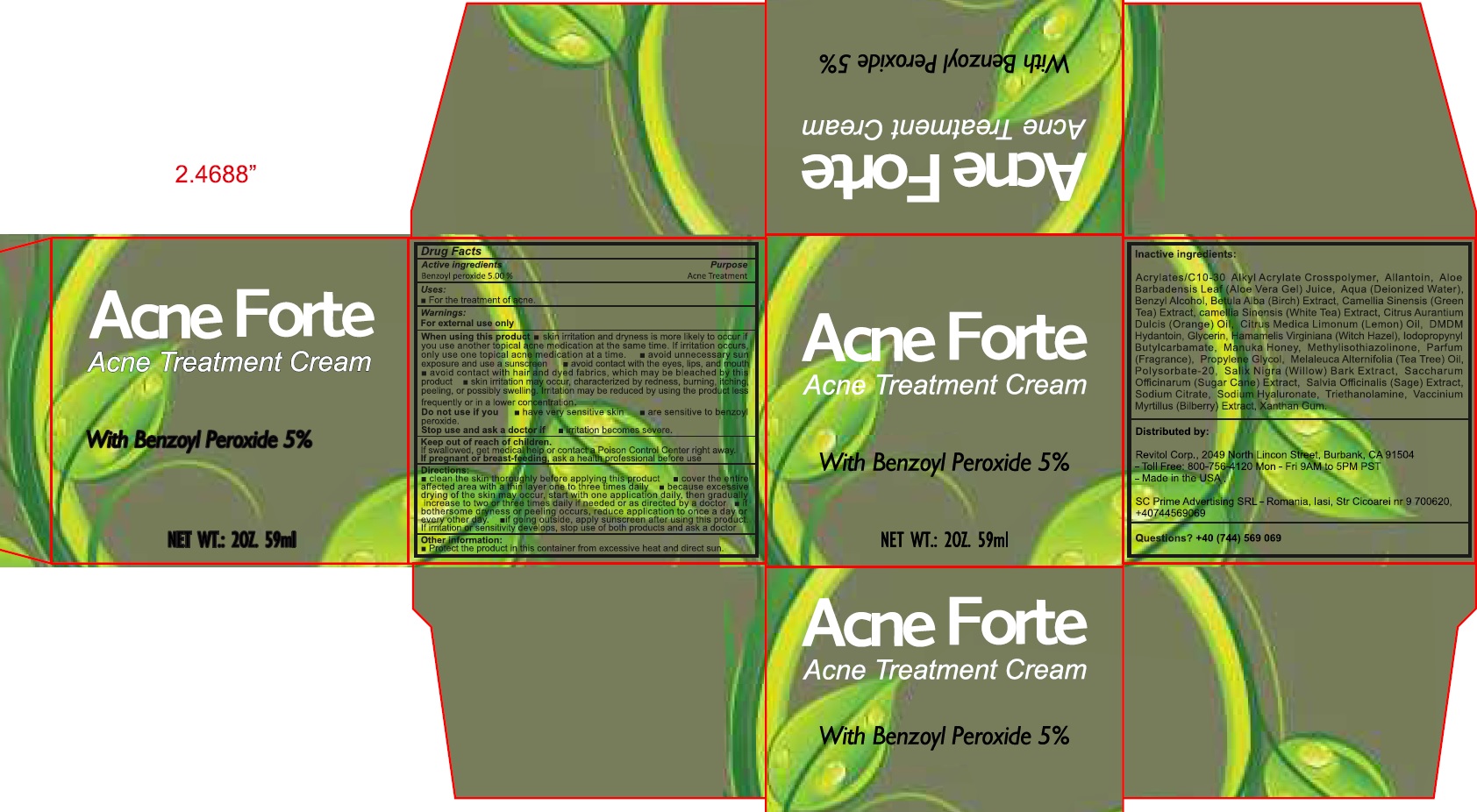 DRUG LABEL: ACNE FORTE Acne Treatment Cream
NDC: 52063-709 | Form: CREAM
Manufacturer: GSCM Ventures Inc. DBA Revitol
Category: otc | Type: HUMAN OTC DRUG LABEL
Date: 20231110

ACTIVE INGREDIENTS: BENZOYL PEROXIDE 50 mg/1 mL
INACTIVE INGREDIENTS: CARBOMER INTERPOLYMER TYPE A (ALLYL SUCROSE CROSSLINKED); ALLANTOIN; ALOE VERA LEAF; WATER; BENZYL ALCOHOL; GREEN TEA LEAF; WHITE TEA; ORANGE OIL, COLD PRESSED; LEMON; DMDM HYDANTOIN; GLYCERIN; HAMAMELIS VIRGINIANA ROOT BARK/STEM BARK; IODOPROPYNYL BUTYLCARBAMATE; METHYLISOTHIAZOLINONE; PROPYLENE GLYCOL; POLYSORBATE 20; SALIX NIGRA BARK; SUGARCANE; SAGE; SODIUM CITRATE; HYALURONATE SODIUM; TROLAMINE; BILBERRY; XANTHAN GUM

ACNE FORTE Acne Treatment Cream

Active ingredients

Benzoyl peroxide 5.00%

Purpose

Acne Treatment

Uses:

- For the treatment of acne.

Warnings:

For external use only

When using this product

- skin irritation and dryness is more likely to occur if you use another topical acne medication at the same time. If irritation occurs, only use one topical acne medication at a time.
- avoid unnecessary sun exposure and use a sunscreen
- avoid contact with the eyes, lips, and mouth
- avoid contact wih hair and dyed fabrics, which may be bleached by this product
- skin irritation may occur, characterized by redness, burning, itching, peeling, or possibly swelling. Irritation may be reduced by using the product less frequently or in a lower concentration.

Do not use if you

- have very sensitive skin
- are sensitive to benzoyl peroxide.

Stop use and ask a doctor if

irritation becomes severe.

Keep out of reach of children.

If swallowed, get medical help or contact a Poison Control Center right away.

If pregnant or breast-feeding,

ask a health professional before use

Directions:

- clean the skin thoroughly before applying this product
- cover the entire affected area with a thin layer one to three times daily.
- because excessive drying of the skin may occur, start with one application daily, then gradually increase to two or three times daily if needed or as directed by a doctor
- if bothersome dryness or peeling occurs, reduce application to once a day or every other day.
- if going outside, apply sunscreen after using this product. If irritation or sensitivity develops, stop use of both products and ask a doctor

Other information:

- Protect the product in this container from excessive heat and direct sun.

Inactive ingredients:

Acrylates/C10-30 Alkyl Acrylate Crosspolymer, Allantoin, ALoe Barbadensis Leaf (Aloe Vera Gel) Juice, Aqua (Deionized Water), Benzyl Alcohol, Betula Alba (Brich) Extract, Camellia Sinensis (Green Tea) Extract, camellia Sinensis (White Tea) Extract, Citrus Aurantium Dulcis (Orange) Oil, Citrus Medica Limonum (Lemon) Oil, DMDM Hydantoin, Glycerin, Hamamelis Virginiana (Witch Hazel), Iodopropynyl Butylcarbamate, Manuka Honey, Methylisothiazolinone, Parfum (Fragrance), Propylene Glycol, Melaleuca Alternifolia (Tea Tree) Oil, Polysorbate-20, Salix Nigra (Willow) Bark Extract, Saccharum Officinarum (Sugar Cane) Extract, Salvia Officinalis (Sage) Extract, Sodium Citrate, Sodium Hyaluronate, Triethanolamine, Vaccinium Myrtillus (Bilberry Extract, Xanthan Gum.

Questions?

+40 (744) 569 069